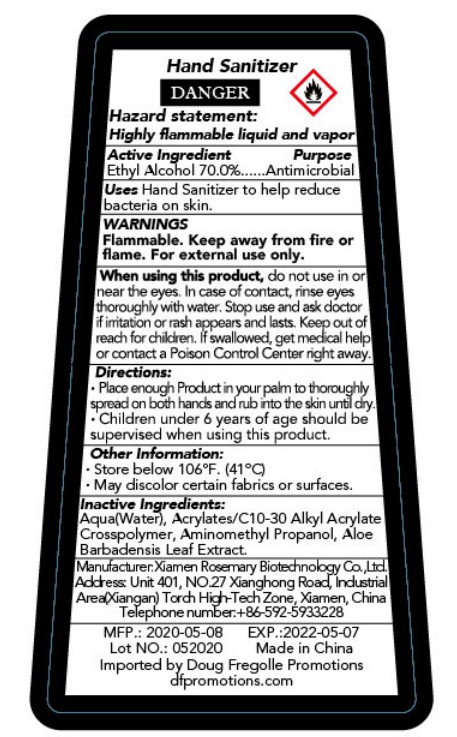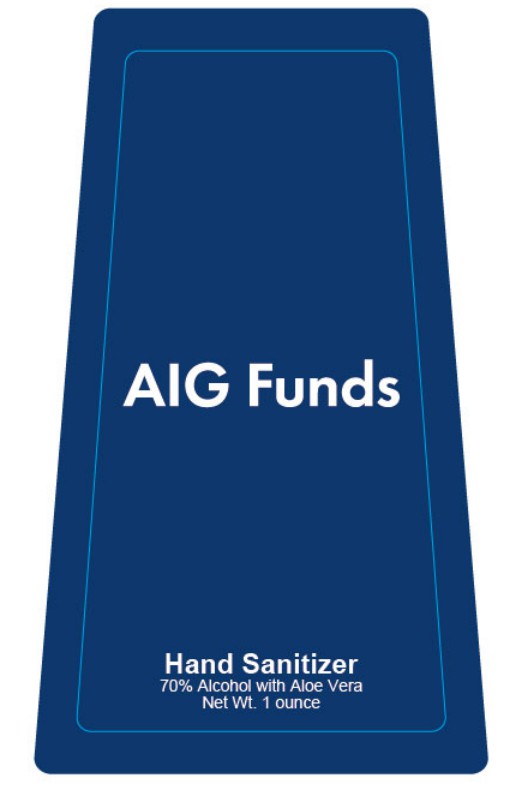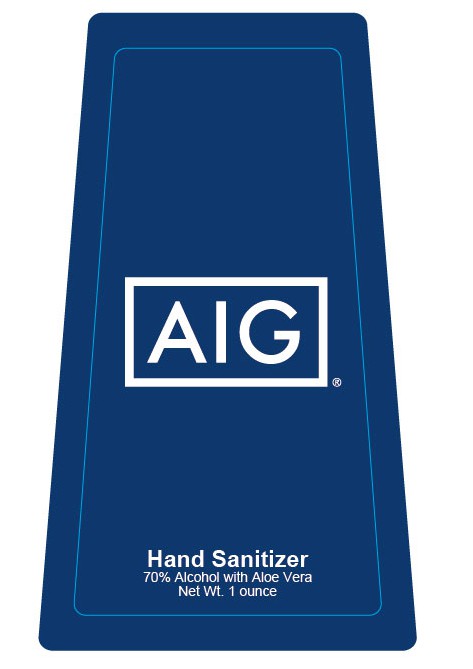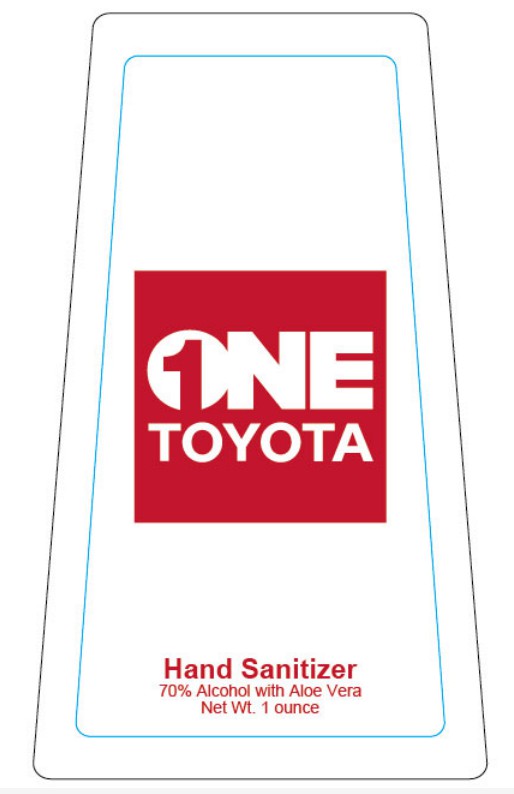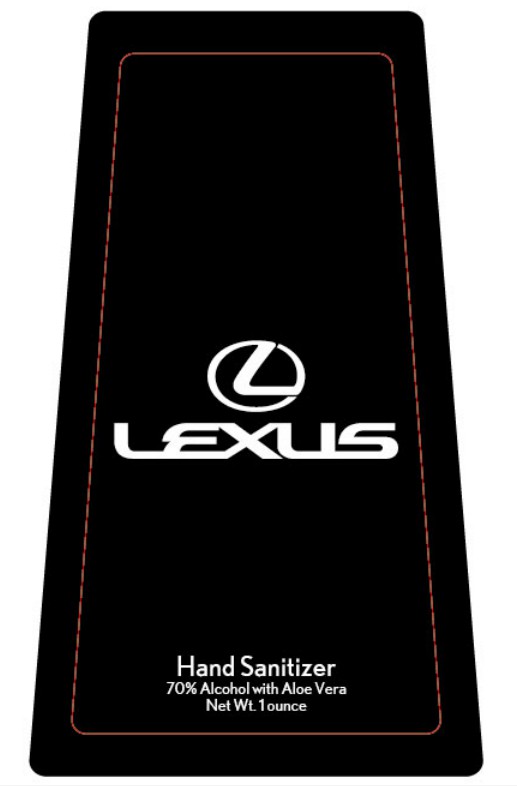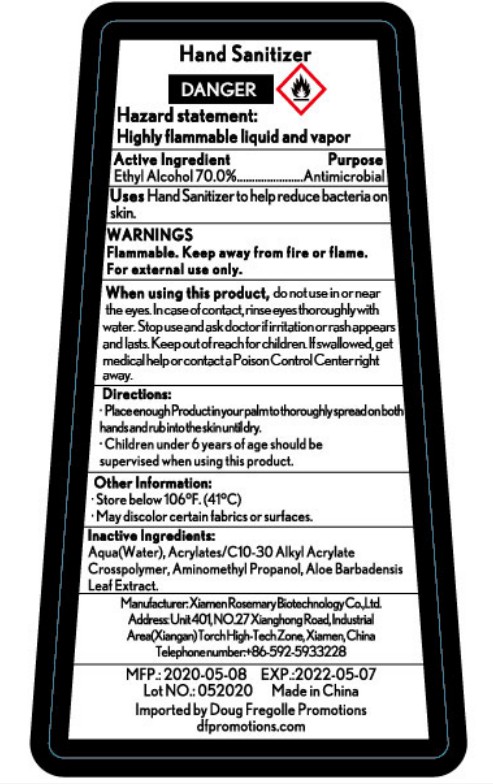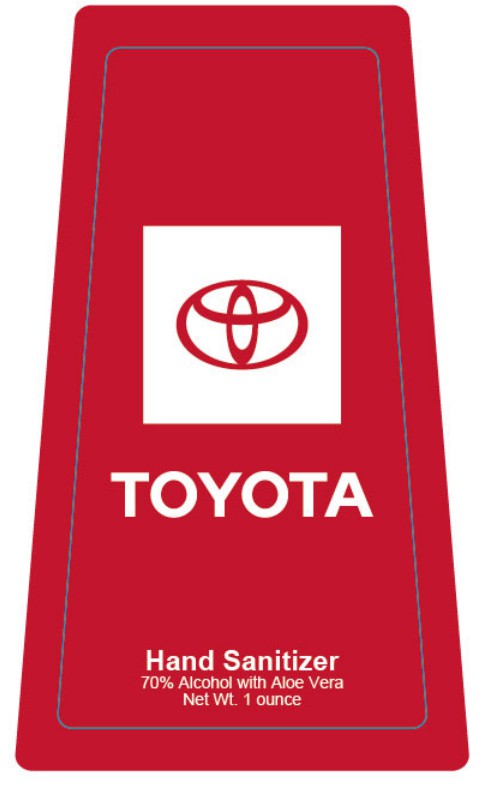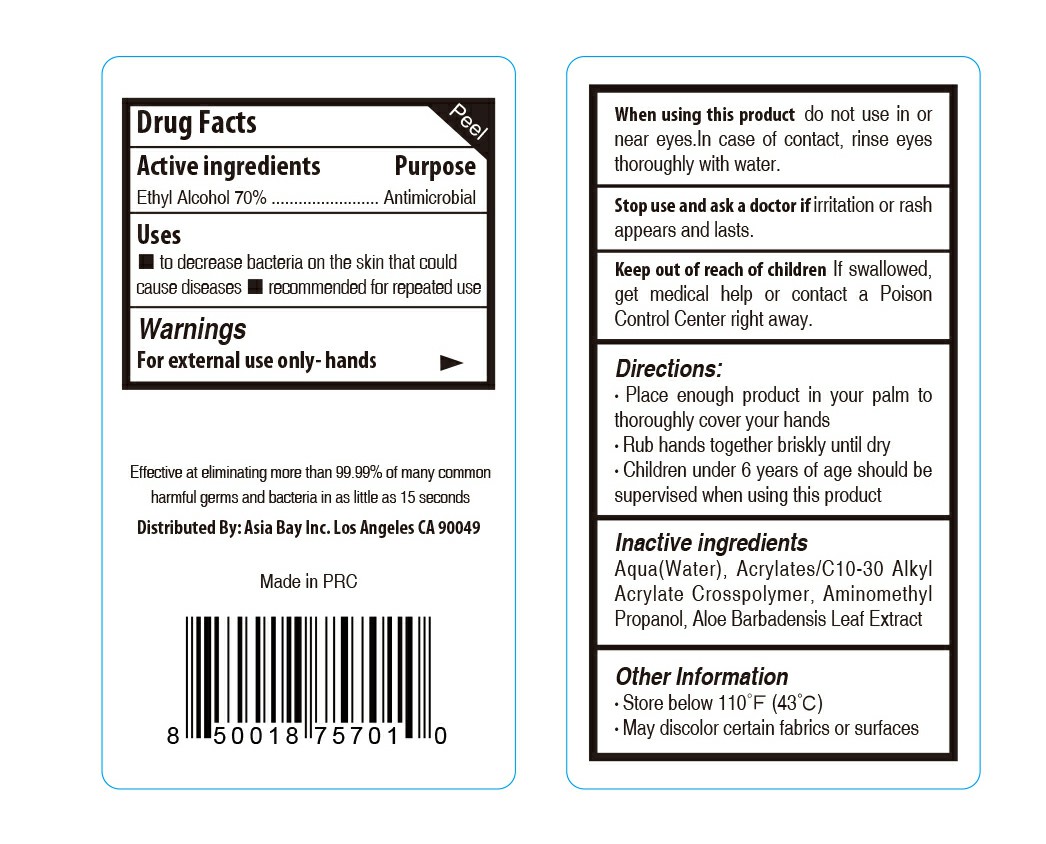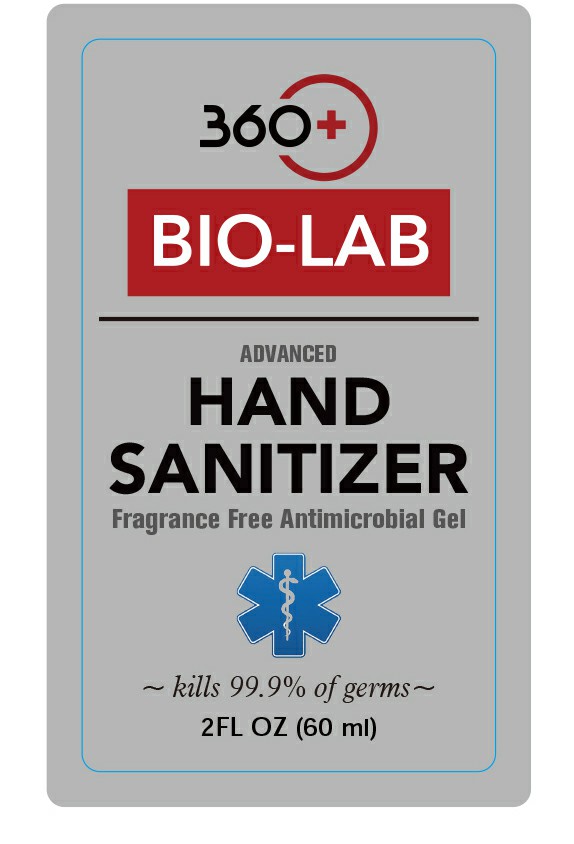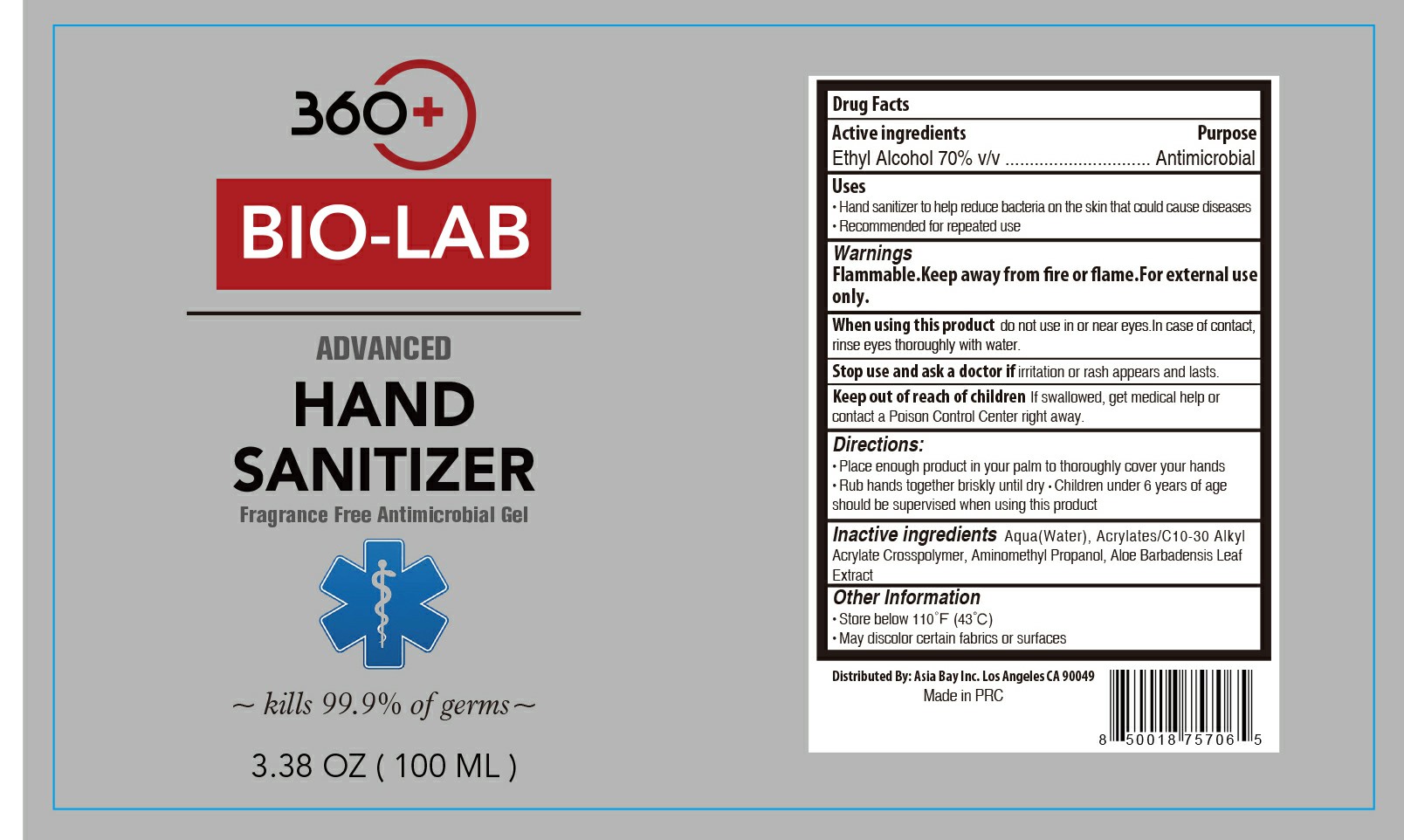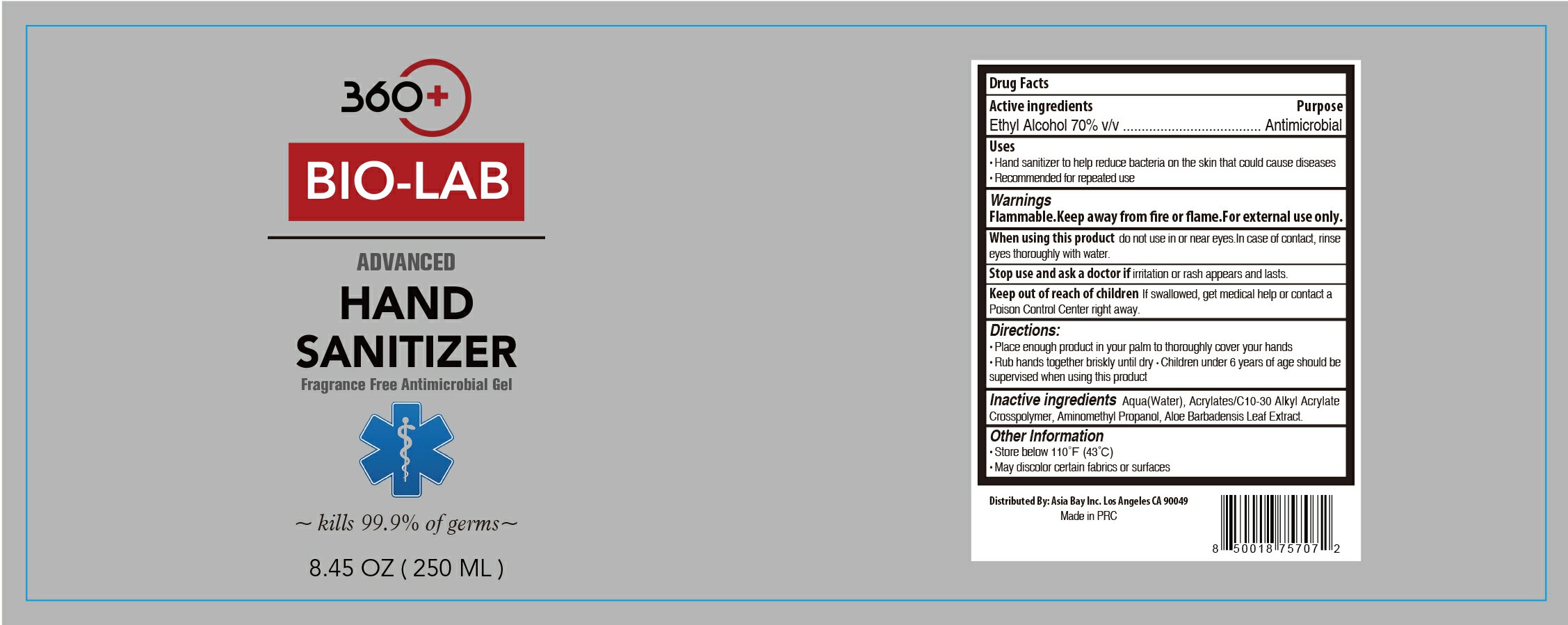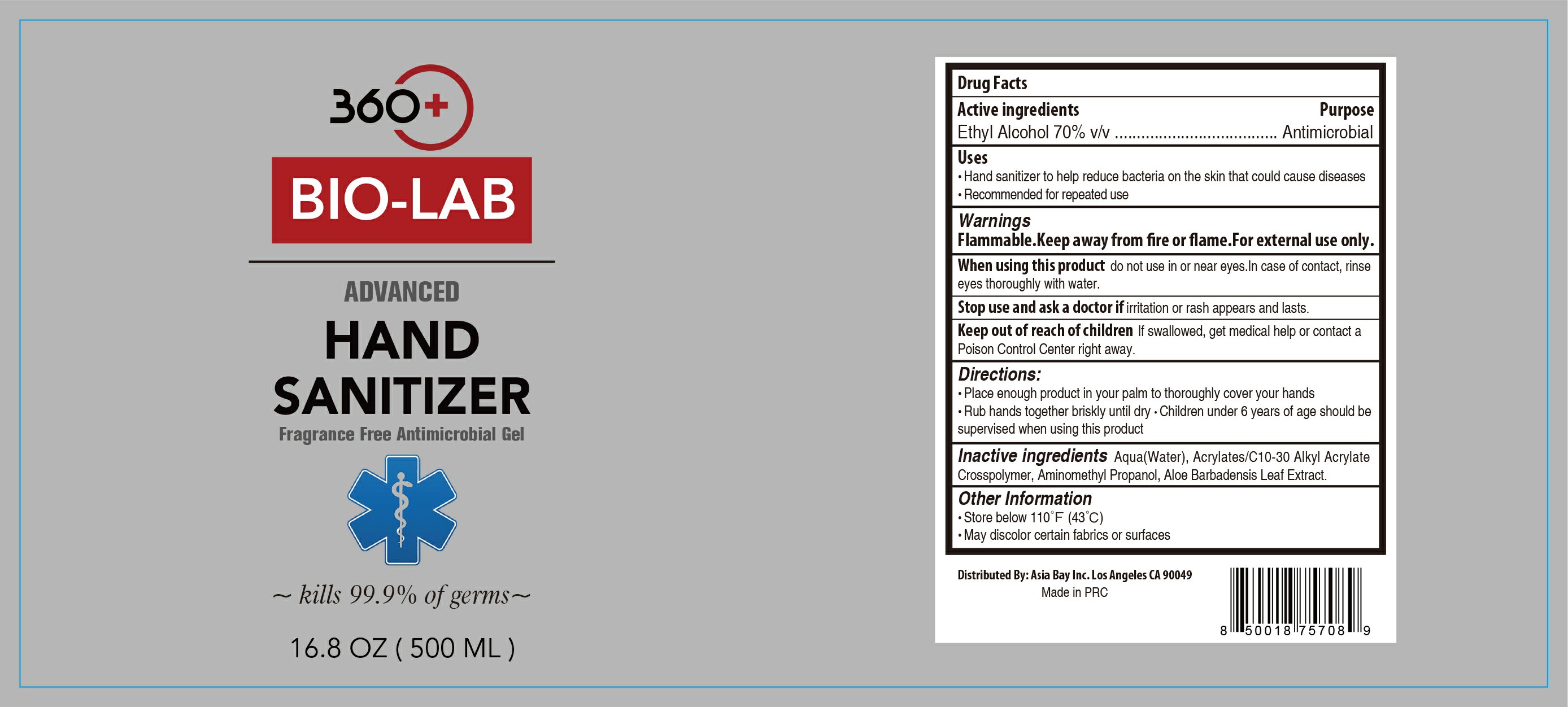 DRUG LABEL: Hand Sanitizer
NDC: 69964-0013 | Form: GEL
Manufacturer: XIAMEN ROSEMARY BIOTECHNOLOGY  CO.,LTD
Category: otc | Type: HUMAN OTC DRUG LABEL
Date: 20200825

ACTIVE INGREDIENTS: ALCOHOL 70 mL/100 mL
INACTIVE INGREDIENTS: ALOE VERA LEAF; WATER; AMINOMETHYLPROPANOL; FRAGRANCE CLEAN ORC0600327; CARBOMER INTERPOLYMER TYPE A (55000 CPS)

69964-0013
Hand Sanitizer

Active Ingredient

Ethyl Alcohol 70.0%

Purpose

Antimicrobial

Uses

Hand Sanitizer to help reduce bacteria on skin.

WARNINGS

Flammable. Keep away from fire or flame.For external use only.

When using this product

do not use in or near the eyes.In case of contact,rinse eyes thoroughly with water.Stop use and ask doctor if irritation or rash appears and lasts.Keep out of reach for children. if swallowed,get medical help or contact a Poison Control Center right away.

Directions

Place enough Product in your palm to thoroughly spread on both hands and rub into the skin until dry.

Children under 6 years of age should be supervised when using this product.

Other information

Store below 106°F.(41°C)

May discolor certain fabrics or surfaces.

Inactive Ingredients

Aqua(Water),Acrylates/C10-30 Alkyl Acrylate Crosspolymer,Parfum(Fragrance),

Aminomethyl Propanol,Aloe Barbadensis Leaf Extract.